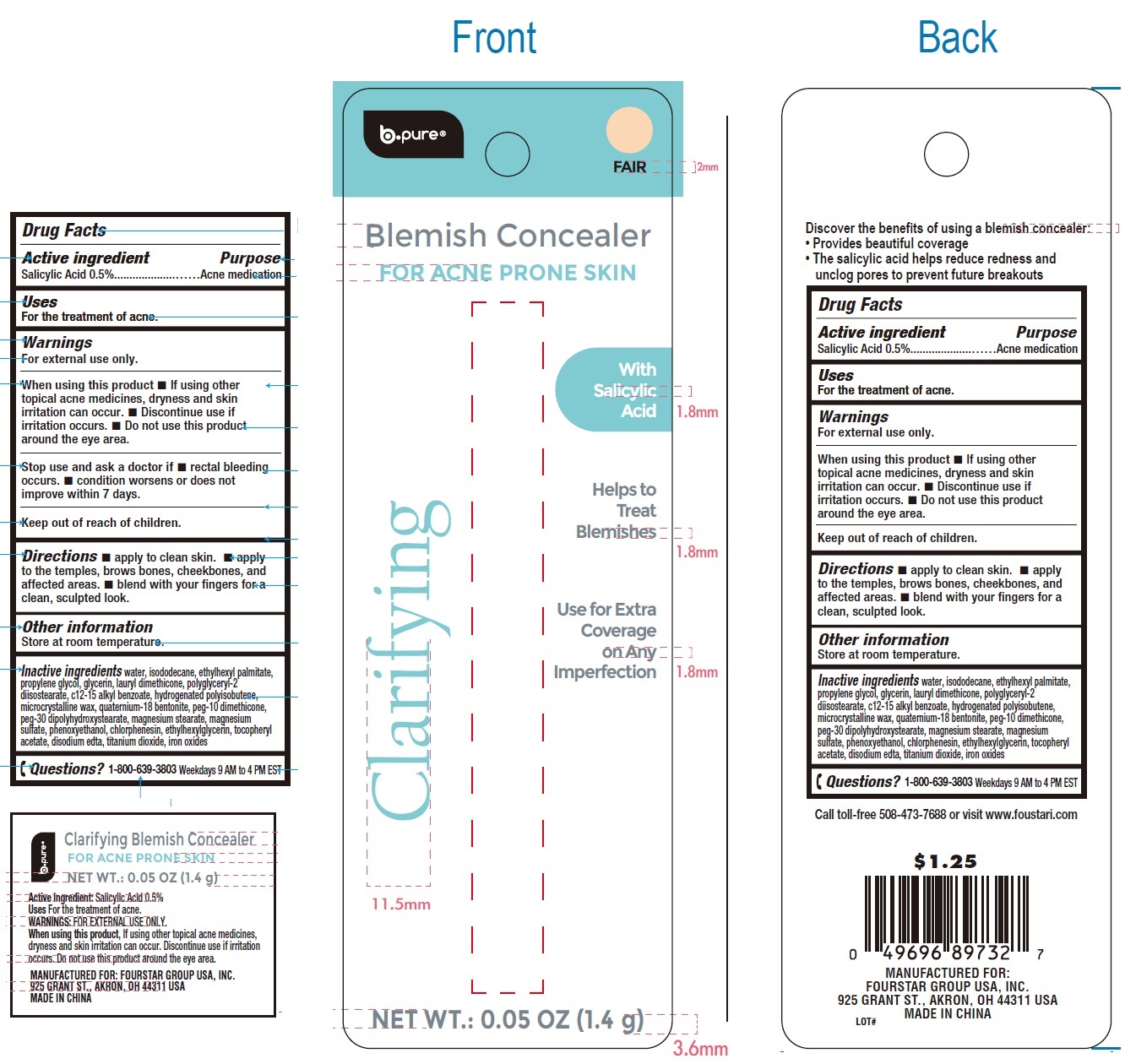 DRUG LABEL: b pure Blemish Concealer for Acne Prone Skin Fair
NDC: 80684-109 | Form: CREAM
Manufacturer: Fourstar Group USA, Inc.
Category: otc | Type: HUMAN OTC DRUG LABEL
Date: 20240611

ACTIVE INGREDIENTS: SALICYLIC ACID 5 mg/1 g
INACTIVE INGREDIENTS: WATER; ISODODECANE; ETHYLHEXYL PALMITATE; PROPYLENE GLYCOL; GLYCERIN; POLYGLYCERYL-2 DIISOSTEARATE; ALKYL (C12-15) BENZOATE; MICROCRYSTALLINE WAX; BENTOQUATAM; PEG-30 DIPOLYHYDROXYSTEARATE (4000 MW); MAGNESIUM STEARATE; MAGNESIUM SULFATE, UNSPECIFIED FORM; PHENOXYETHANOL; CHLORPHENESIN; ETHYLHEXYLGLYCERIN; .ALPHA.-TOCOPHEROL ACETATE; EDETATE DISODIUM; TITANIUM DIOXIDE; FERRIC OXIDE RED

b.pure Blemish Concealer for Acne Prone Skin, Fair

Active ingredient

Salicylic Acid 0.5%

Purpose

Acne medication

Uses

For the treatment of acne.

Warnings

For external use only.

When using this product

- If using other topical acne medicines, dryness and skin irritation can occur.
- Discontinue use if irritation occurs.
- Do not use this product around the eye area.

Stop use and ask a doctor if

- rectal bleeding occurs.
- condition worsens or does not improve within 7 days.

Directions

- apply to clean skin.
- apply to the temples, brows bones, cheekbones, and affected areas.
- blend with your fingers for a clean, sculpted look.

Other information

Store at room temperature.

Inactive ingredients

water, isododecane, ethylhexyl palmitate, propylene glycol, glycerin, lauryl dimethicone, polyglyceryl-2 diisostearate, c12-15 alkyl benzoate, hydrogenated polyisobutene, microcrystalline wax, quaternium-18 bentonite, peg-10 dimethicone, peg-30 dipolyhydroxystearate, magnesium stearate, magnesium sulfate, phenoxyethanol, chlorphenesin, ethylhexylglycerin, tocopheryl acetate, disodium edta, titanium dioxide, iron oxides

Questions?

1-800-639-3803 Weekdays 9 AM to 4 PM EST

Call toll-free 508-473-7688 or visit www.foustari.com